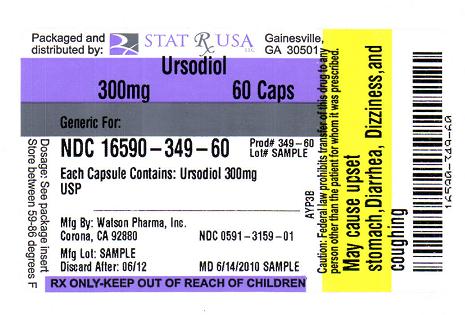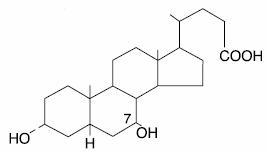 DRUG LABEL: URSODIOL
NDC: 16590-349 | Form: CAPSULE
Manufacturer: STAT RX USA LLC
Category: prescription | Type: HUMAN PRESCRIPTION DRUG LABEL
Date: 20100614

ACTIVE INGREDIENTS: URSODIOL 300 mg/1 1
INACTIVE INGREDIENTS: COLLOIDAL SILICON DIOXIDE; FERRIC OXIDE; GELATIN; MAGNESIUM STEARATE; STARCH, CORN; FERROSOFERRIC OXIDE

Ursodiol Capsules USP
Revised: August 2008
Rx only
2000700-00

Prescribing Information

SPECIAL NOTE
Gallbladder stone dissolution with ursodiol treatment requires months of therapy. Complete dissolution does not occur in all patients and recurrence of stones within 5 years has been observed in up to 50% of patients who do dissolve their stones on bile acid therapy. Patients should be carefully selected for therapy with ursodiol, and alternative therapies should be considered.

DESCRIPTION

Ursodiol is a bile acid available as 300 mg capsules suitable for oral administration.

Ursodiol USP (ursodeoxycholic acid) is a naturally occurring bile acid found in small quantities in normal human bile and in the biles of certain other mammals. It is a bitter-tasting, white powder freely soluble in ethanol, methanol, and glacial acetic acid; sparingly soluble in chloroform; slightly soluble in ether; and insoluble in water. The chemical name for ursodiol is 3α,7β-Dihydroxy-5β-cholan-24-oic acid (C24H40O4). Ursodiol, USP has a molecular weight of 392.57. Its structure is shown below:

Inactive Ingredients: Colloidal silicon dioxide, magnesium stearate, and starch (corn). Gelatin capsules contain gelatin and titanium dioxide. The capsules are printed with edible ink containing black iron oxide.

CLINICAL PHARMACOLOGY

About 90% of a therapeutic dose of ursodiol is absorbed in the small bowel after oral administration. After absorption, ursodiol enters the portal vein and undergoes efficient extraction from portal blood by the liver (i.e., there is a large “first-pass” effect) where it is conjugated with either glycine or taurine and is then secreted into the hepatic bile ducts. Ursodiol in bile is concentrated in the gallbladder and expelled into the duodenum in gallbladder bile via the cystic and common ducts by gallbladder contractions provoked by physiologic responses to eating. Only small quantities of ursodiol appear in the systemic circulation and very small amounts are excreted into urine. The sites of the drug’s therapeutic actions are in the liver, bile, and gut lumen.

Beyond conjugation, ursodiol is not altered or catabolized appreciably by the liver or intestinal mucosa. A small proportion of orally administered drug undergoes bacterial degradation with each cycle of enterohepatic circulation. Ursodiol can be both oxidized and reduced at the 7-carbon, yielding either 7-keto-lithocholic acid or lithocholic acid, respectively. Further, there is some bacterially catalyzed deconjugation of glyco- and tauro- ursodeoxycholic acid in the small bowel. Free ursodiol, 7-keto-lithocholic acid, and lithocholic acid are relatively insoluble in aqueous media and larger proportions of these compounds are lost from the distal gut into the feces. Reabsorbed free ursodiol is reconjugated by the liver. Eighty percent of lithocholic acid formed in the small bowel is excreted in the feces, but the 20% that is absorbed is sulfated at the 3-hydroxyl group in the liver to relatively insoluble lithocholyl conjugates which are excreted into bile and lost in feces. Absorbed 7-keto-lithocholic acid is stereospecifically reduced in the liver to chenodiol.

Lithocholic acid causes cholestatic liver injury and can cause death from liver failure in certain species unable to form sulfate conjugates. Lithocholic acid is formed by 7-dehydroxylation of the dihydroxy bile acids (ursodiol and chenodiol) in the gut lumen. The 7-dehydroxylation reaction appears to be alpha-specific, i.e., chenodiol is more efficiently 7-dehydroxylated than ursodiol and, for equimolar doses of ursodiol and chenodiol, levels of lithocholic acid appearing in bile are lower with the former. Man has the capacity to sulfate lithocholic acid. Although liver injury has not been associated with ursodiol therapy, a reduced capacity to sulfate may exist in some individuals, but such a deficiency has not yet been clearly demonstrated.

Pharmacodynamics

Ursodiol suppresses hepatic synthesis and secretion of cholesterol, and also inhibits intestinal absorption of cholesterol. It appears to have little inhibitory effect on synthesis and secretion into bile of endogenous bile acids, and does not appear to affect secretion of phospholipids into bile.

With repeated dosing, bile ursodeoxycholic acid concentrations reach a steady state in about 3 weeks. Although insoluble in aqueous media, cholesterol can be solubilized in at least two different ways in the presence of dihydroxy bile acids. In addition to solubilizing cholesterol in micelles, ursodiol acts by an apparently unique mechanism to cause dispersion of cholesterol as liquid crystals in aqueous media. Thus, even though administration of high doses (e.g., 15-18 mg/kg/day) does not result in a concentration of ursodiol higher than 60% of the total bile acid pool, ursodiol-rich bile effectively solubilizes cholesterol. The overall effect of ursodiol is to increase the concentration level at which saturation of cholesterol occurs.

The various actions of ursodiol combine to change the bile of patients with gallstones from cholesterol-precipitating to cholesterol-solubilizing, thus resulting in bile conducive to cholesterol stone dissolution.

After ursodiol dosing is stopped, the concentration of the bile acid in bile falls exponentially, declining to about 5%-10% of its steady-state level in about 1 week.

Clinical Results

Gallstone Dissolution
On the basis of clinical trial results in a total of 868 patients with radiolucent gallstones treated in 8 studies (three in the U.S. involving 282 patients, one in the U.K. involving 130 patients, and four in Italy involving 456 patients) for periods ranging from 6-78 months with ursodiol doses ranging from about 5-20 mg/kg/day, an ursodiol dose of about 8-10 mg/kg/day appeared to be the best dose. With an ursodiol dose of about 10 mg/kg/day, complete stone dissolution can be anticipated in about 30% of unselected patients with uncalcified gallstones < 20 mm in maximal diameter treated for up to 2 years. Patients with calcified gallstones prior to treatment, or patients who develop stone calcification or gallbladder nonvisualization on treatment, and patients with stones > 20 mm in maximal diameter rarely dissolve their stones. The chance of gallstone dissolution is increased up to 50% in patients with floating or floatable stones (i.e., those with high cholesterol content), and is inversely related to stone size for those < 20 mm in maximal diameter. Complete dissolution was observed in 81% of patients with stones up to 5 mm in diameter. Age, sex, weight, degree of obesity, and serum cholesterol level are not related to the chance of stone dissolution with ursodiol.

A nonvisualizing gallbladder by oral cholecystogram prior to the initiation of therapy is not a contraindication to ursodiol therapy (the group of patients with nonvisualizing gallbladders in the ursodiol studies had complete stone dissolution rates similar to the group of patients with visualizing gallbladders). However, gallbladder nonvisualization developing during ursodiol treatment predicts failure of complete stone dissolution and in such cases therapy should be discontinued.

Partial stone dissolution occurring within 6 months of beginning therapy with ursodiol appears to be associated with a >70% chance of eventual complete stone dissolution with further treatment; partial dissolution observed within 1 year of starting therapy indicates a 40% probability of complete dissolution.

Stone recurrence after dissolution with ursodiol therapy was seen within 2 years in 8/27 (30%) of patients in the U.K. studies. Of 16 patients in the U.K. study whose stones had previously dissolved on chenodiol but later recurred, 11 had complete dissolution on ursodiol. Stone recurrence has been observed in up to 50% of patients within 5 years of complete stone dissolution on ursodiol therapy. Serial ultrasonographic examinations should be obtained to monitor for recurrence of stones, bearing in mind that radiolucency of the stones should be established before another course of ursodiol is instituted. A prophylactic dose of ursodiol has not been established.

Gallstone Prevention
Two placebo-controlled, multicenter, double-blind, randomized, parallel group trials in a total of 1,316 obese patients were undertaken to evaluate ursodiol in the prevention of gallstone formation in obese patients undergoing rapid weight loss. The first trial consisted of 1,004 obese patients with a body mass index (BMI) ≥ 38 who underwent weight loss induced by means of a very low calorie diet for a period of 16 weeks. An intent-to-treat analysis of this trial showed that gallstone formation occurred in 23% of the placebo group, while those patients on 300, 600, or 1200 mg/day of ursodiol experienced a 6%, 3%, and 2% incidence of gallstone formation, respectively. The mean weight loss for this 16-week trial was 47 lb for the placebo group, and 47, 48, and 50 lb for the 300, 600, and 1200 mg/day ursodiol groups, respectively.

The second trial consisted of 312 obese patients (BMI ≥ 40) who underwent rapid weight loss through gastric bypass surgery. The trial drug treatment period was for 6 months following this surgery. Results of this trial showed that gallstone formation occurred in 23% of the placebo group, while those patients on 300, 600, or 1200 mg/day of ursodiol experienced a 9%, 1%, and 5% incidence of gallstone formation, respectively. The mean weight loss for this 6-month trial was 64 lb for the placebo group, and 67, 74, and 72 lb for the 300, 600, and 1200 mg/day ursodiol groups, respectively.

ALTERNATIVE THERAPIES

Watchful Waiting

Watchful waiting has the advantage that no therapy may ever be required. For patients with silent or minimally symptomatic stones, the rate of development of moderate-to-severe symptoms or gallstone complications is estimated to be between 2% and 6% per year, leading to a cumulative rate of 7%-27% in 5 years. Presumably the rate is higher for patients already having symptoms.

Cholecystectomy

For patients with symptomatic gallstones, surgery offers the advantage of immediate and permanent stone removal, but carries a high risk in some patients. About 5% of cholecystectomized patients have residual symptoms or retained common duct stones. The spectrum of surgical risk varies as a function of age and the presence of disease other than cholelithiasis.

Mortality Rates for Cholecystectomy in the U.S. (National Halothane Study, JAMA 1966; 197:775-8) 27,600 Cholecystectomies (Smoothed Rates) Deaths/1000 Operations***
 | Age (Yrs) | Cholecystectomy | Cholecystectomy+ Common Duct Exploration
Low Risk Patients*
Women | 0-49 | .54 | 2.13
 | 50-69 | 2.80 | 10.10
Men | 0-49 | 1.04 | 4.12
 | 50-69 | 5.41 | 19.23
High Risk Patients**
Women | 0-49 | 12.66 | 47.62
 | 50-69 | 17.24 | 58.82
Men | 0-49 | 24.39 | 90.91
 | 50-69 | 33.33 | 111.11
* In good health or with moderate systemic disease.
** With severe or extreme systemic disease.
*** Includes both elective and emergency surgery.

Women in good health or who have only moderate systemic disease and are under 49 years of age have the lowest surgical mortality rate (0.054); men in all categories have a surgical mortality rate twice that of women. Common duct exploration quadruples the rates in all categories. The rates rise with each decade of life and increase tenfold or more in all categories with severe or extreme systemic disease.

INDICATIONS AND USAGE

1. Ursodiol is indicated for patients with radiolucent, noncalcified gallbladder stones < 20 mm in greatest diameter in whom elective cholecystectomy would be undertaken except for the presence of increased surgical risk due to systemic disease, advanced age, idiosyncratic reaction to general anesthesia, or for those patients who refuse surgery. Safety of use of ursodiol beyond 24 months is not established.
2. Ursodiol is indicated for the prevention of gallstone formation in obese patients experiencing rapid weight loss.

CONTRAINDICATIONS

1. Ursodiol will not dissolve calcified cholesterol stones, radiopaque stones, or radiolucent bile pigment stones. Hence, patients with such stones are not candidates for ursodiol therapy.
2. Patients with compelling reasons for cholecystectomy including unremitting acute cholecystitis, cholangitis, biliary obstruction, gallstone pancreatitis, or biliary-gastrointestinal fistula are not candidates for ursodiol therapy.
3. Allergy to bile acids.

PRECAUTIONS

Liver Tests

Ursodiol therapy has not been associated with liver damage. Lithocholic acid, a naturally occurring bile acid, is known to be a liver-toxic metabolite. This bile acid is formed in the gut from ursodiol less efficiently and in smaller amounts than that seen from chenodiol.

Lithocholic acid is detoxified in the liver by sulfation and, although man appears to be an efficient sulfater, it is possible that some patients may have a congenital or acquired deficiency in sulfation, thereby predisposing them to lithocholate-induced liver damage.

Abnormalities in liver enzymes have not been associated with ursodiol therapy and, in fact, ursodiol has been shown to decrease liver enzyme levels in liver disease. However, patients given ursodiol should have SGOT (AST) and SGPT (ALT) measured at the initiation of therapy and thereafter as indicated by the particular clinical circumstances.

Drug Interactions

Bile acid sequestering agents such as cholestyramine and colestipol may interfere with the action of ursodiol by reducing its absorption. Aluminum-based antacids have been shown to adsorb bile acids in vitro and may be expected to interfere with ursodiol in the same manner as the bile acid sequestering agents. Estrogens, oral contraceptives, and clofibrate (and perhaps other lipid-lowering drugs) increase hepatic cholesterol secretion, and encourage cholesterol gallstone formation and hence may counteract the effectiveness of ursodiol.

Carcinogenesis, Mutagenesis, Impairment of Fertility

Ursodeoxycholic acid was tested in 2-year oral carcinogenicity studies in CD-1 mice and Sprague-Dawley rats at daily doses of 50, 250, and 1000 mg/kg/day. It was not tumorigenic in mice. In the rat study, it produced statistically significant dose-related increased incidences of pheochromocytomas of adrenal medulla in males (p=0.014, Peto trend test) and females (p=0.004, Peto trend test). A 78-week rat study employing intrarectal instillation of lithocholic acid and tauro-deoxycholic acid, metabolites of ursodiol and chenodiol, has been conducted. These bile acids alone did not produce any tumors. A tumor-promoting effect of both metabolites was observed when they were co-administered with a carcinogenic agent. Results of epidemiologic studies suggest that bile acids might be involved in the pathogenesis of human colon cancer in patients who had undergone a cholecystectomy, but direct evidence is lacking. Ursodiol is not mutagenic in the Ames test. Dietary administration of lithocholic acid to chickens is reported to cause hepatic adenomatous hyperplasia.

Pregnancy Category B

Reproduction studies have been performed in rats and rabbits with ursodiol doses up to 200-fold the therapeutic dose and have revealed no evidence of impaired fertility or harm to the fetus at doses of 20- to 100-fold the human dose in rats and at 5-fold the human dose (highest dose tested) in rabbits. Studies employing 100- to 200-fold the human dose in rats have shown some reduction in fertility rate and litter size. There have been no adequate and well-controlled studies of the use of ursodiol in pregnant women, but inadvertent exposure of 4 women to therapeutic doses of the drug in the first trimester of pregnancy during the ursodiol trials led to no evidence of effects on the fetus or newborn baby. Although it seems unlikely, the possibility that ursodiol can cause fetal harm cannot be ruled out; hence, the drug is not recommended for use during pregnancy.

Nursing Mothers

It is not known whether ursodiol is excreted in human milk. Because many drugs are excreted in human milk, caution should be exercised when ursodiol is administered to a nursing mother.

Pediatric Use

The safety and effectiveness of ursodiol in pediatric patients have not been established.

Geriatric Use

In worldwide clinical studies of ursodiol, approximately 14% of subjects were over 65 years of age (approximately 3% were over 75 years old). In a subgroup analysis of existing clinical trials, patients greater than 56 years of age did not exhibit statistically significantly different complete dissolution rates from the younger population. No age-related differences in safety and effectiveness were found. Other reported clinical experience has not identified differences in response in elderly and younger patients. However, small differences in efficacy and greater sensitivity of some elderly individuals taking ursodiol cannot be ruled out. Therefore, it is recommended that dosing proceed with caution in this population.

ADVERSE REACTIONS

The nature and frequency of adverse experiences were similar across all groups.

The following tables provide comprehensive listings of the adverse experiences reported that occurred with a 5% incidence level:

GALLSTONE DISSOLUTION
 | Ursodiol |  | Placebo
 | 8-10 mg/kg/day
 | (N=155) |  | (N=159)
 | N | (%) | N | (%)
Body as a Whole
Allergy | 8 | (5.2) | 7 | (4.4)
Chest Pain | 5 | (3.2) | 10 | (6.3)
Fatigue | 7 | (4.5) | 8 | (5.0)
Infection Viral | 30 | (19.4) | 41 | (25.8)
Digestive System
Abdominal Pain | 67 | (43.2) | 70 | (44.0)
Cholecystitis | 8 | (5.2) | 7 | (4.4)
Constipation | 15 | (9.7) | 14 | (8.8)
Diarrhea | 42 | (27.1) | 34 | (21.4)
Dyspepsia | 26 | (16.8) | 18 | (11.3)
Flatulence | 12 | (7.7) | 12 | (7.5)
Gastrointestinal Disorder | 6 | (3.9) | 8 | (5.0)
Nausea | 22 | (14.2) | 27 | (17.0)
Vomiting | 15 | (9.7) | 11 | (6.9)
Musculoskeletal System
Arthralgia | 12 | (7.7) | 24 | (15.1)
Arthritis | 9 | (5.8) | 4 | (2.5)
Back Pain | 11 | (7.1) | 18 | (11.3)
Myalgia | 9 | (5.8) | 9 | (5.7)
Nervous System
Headache | 28 | (18.1) | 34 | (21.4)
Insomnia | 3 | (1.9) | 8 | (5.0)
Respiratory System
Bronchitis | 10 | (6.5) | 6 | (3.8)
Coughing | 11 | (7.1) | 7 | (4.4)
Pharyngitis | 13 | (8.4) | 5 | (3.1)
Rhinitis | 8 | (5.2) | 11 | (6.9)
Sinusitis | 17 | (11.0) | 18 | (11.3)
Upper Respiratory
Tract Infection | 24 | (15.5) | 21 | (13.2)
Urogenital System
Urinary Tract Infection | 10 | (6.5) | 7 | (4.4)

GALLSTONE PREVENTION
 | Ursodiol |  | Placebo
 | 600 mg
 | (N=322) |  | (N=325)
 | N | (%) | N | (%)
Body as a Whole
Fatigue | 25 | (7.8) | 33 | (10.2)
Infection Viral | 29 | (9.0) | 29 | (8.9)
Influenza-like Symptoms | 21 | (6.5) | 19 | (5.8)
Digestive System
Abdominal Pain | 20 | (6.2) | 39 | (12.0)
Constipation | 85 | (26.4) | 72 | (22.2)
Diarrhea | 81 | (25.2) | 68 | (20.9)
Flatulence | 15 | (4.7) | 24 | (7.4)
Nausea | 56 | (17.4) | 43 | (13.2)
Vomiting | 44 | (13.7) | 44 | (13.5)
Musculoskeletal System
Back Pain | 38 | (11.8) | 21 | (6.5)
Musculoskeletal Pain | 19 | (5.9) | 15 | (4.6)
Nervous System
Dizziness | 53 | (16.5) | 42 | (12.9)
Headache | 80 | (24.8) | 78 | (24.0)
Respiratory System
Pharyngitis | 10 | (3.1) | 19 | (5.8)
Sinusitis | 17 | (5.3) | 18 | (5.5)
Upper Respiratory
Tract Infection | 40 | (12.4) | 35 | (10.8)
Skin and Appendages
Alopecia | 17 | (5.3) | 8 | (2.5)
Urogenital System
Dysmenorrhea | 18 | (5.6) | 19 | (5.8)

OVERDOSAGE

Neither accidental nor intentional overdosing with ursodiol has been reported. Doses of ursodiol in the range of 16-20 mg/kg/day have been tolerated for 6-37 months without symptoms by 7 patients. The LD50 for ursodiol in rats is over 5000 mg/kg given over 7-10 days and over 7500 mg/kg for mice. The most likely manifestation of severe overdose with ursodiol would probably be diarrhea, which should be treated symptomatically.

DOSAGE AND ADMINISTRATION

Gallstone Dissolution

The recommended dose for ursodiol treatment of radiolucent gallbladder stones is 8-10 mg/kg/day given in 2 or 3 divided doses.

Ultrasound images of the gallbladder should be obtained at 6-month intervals for the first year of ursodiol therapy to monitor gallstone response. If gallstones appear to have dissolved, ursodiol therapy should be continued and dissolution confirmed on a repeat ultrasound examination within 1-3 months. Most patients who eventually achieve complete stone dissolution will show partial or complete dissolution at the first on-treatment reevaluation. If partial stone dissolution is not seen by 12 months of ursodiol therapy, the likelihood of success is greatly reduced.

Gallstone Prevention

The recommended dosage of ursodiol for gallstone prevention in patients undergoing rapid weight loss is 600 mg/day (300 mg b.i.d.).

HOW SUPPLIED

Ursodiol Capsules USP, 300 mg are opaque white capsules imprinted WATSON on one half and 3159 on the other half of the capsule in black. Bottles of 100 are supplied with child-resistant closures.

Store at 25°C (77°F); excursions permitted to 15°-30°C (59°-86°F).
Dispense in a tight container (USP).

Rx only

Keep out of reach of children.

Manufactured By:
Watson Pharma Private Limited
Verna, Salcette Goa 403 722 INDIA

Distributed By:
Watson Pharma, Inc.
Corona, CA 92880 USA

Revised: August 2008

2000700-00
S0808

URSODIOL 300MG LABEL IMAGE